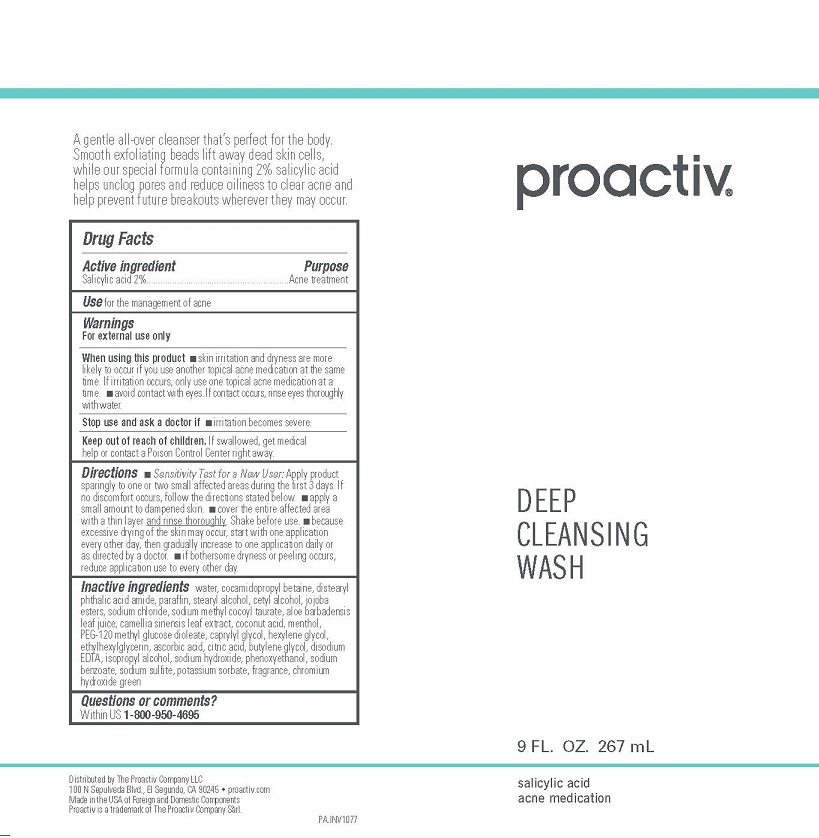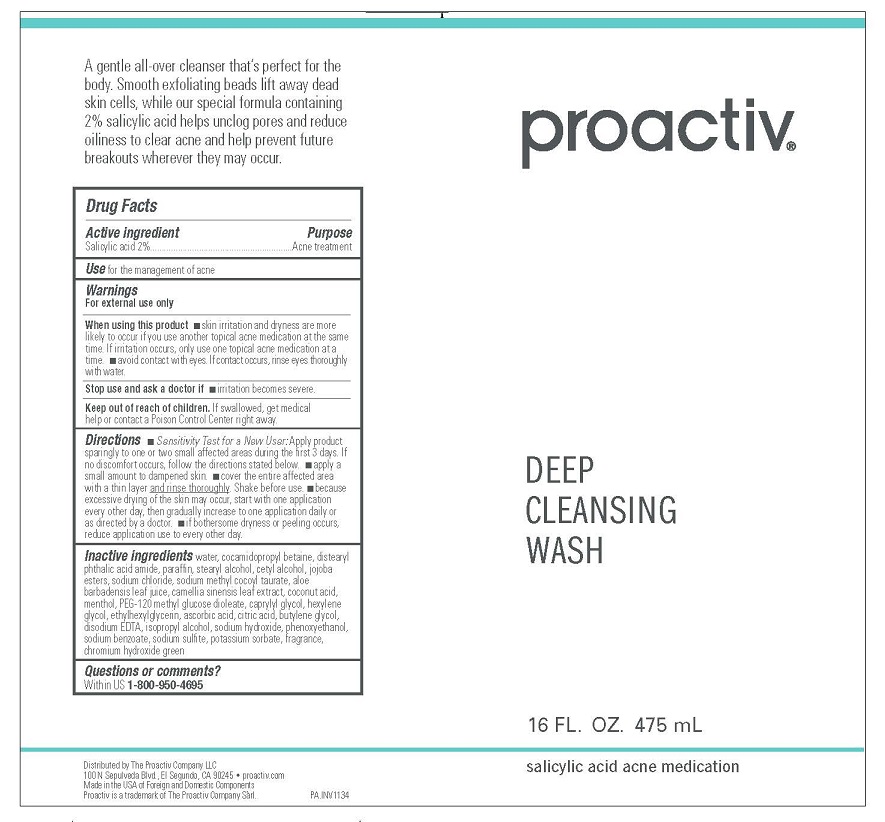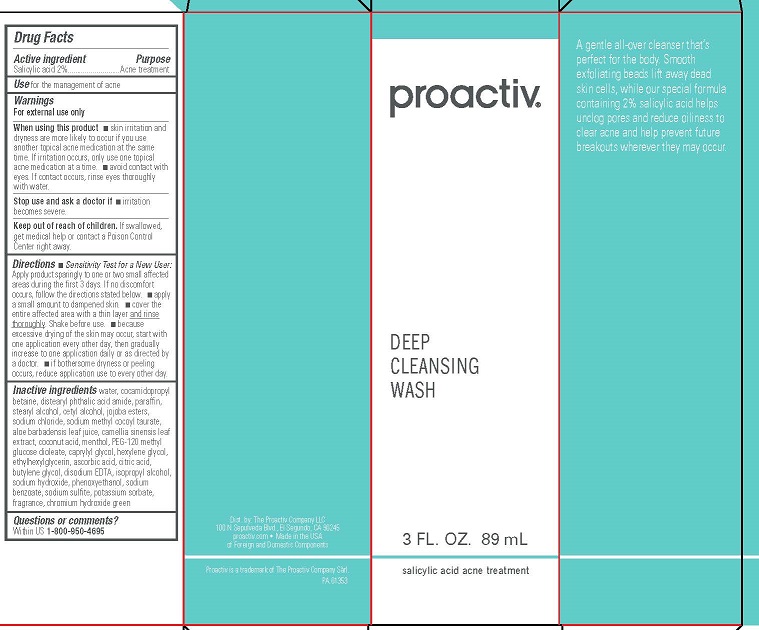 DRUG LABEL: Proactiv Deep Cleansing Wash
NDC: 11410-048 | Form: LOTION/SHAMPOO
Manufacturer: THE PROACTIV COMPANY LLC
Category: otc | Type: HUMAN OTC DRUG LABEL
Date: 20260107

ACTIVE INGREDIENTS: SALICYLIC ACID 2 g/100 mL
INACTIVE INGREDIENTS: WATER; COCAMIDOPROPYL BETAINE; DISTEARYL PHTHALAMIC ACID; PARAFFIN; STEARYL ALCOHOL; CETYL ALCOHOL; SODIUM CHLORIDE; SODIUM METHYL COCOYL TAURATE; ALOE VERA LEAF; GREEN TEA LEAF; COCONUT ACID; MENTHOL; PEG-120 METHYL GLUCOSE DIOLEATE; CAPRYLYL GLYCOL; HEXYLENE GLYCOL; ETHYLHEXYLGLYCERIN; ASCORBIC ACID; CITRIC ACID MONOHYDRATE; BUTYLENE GLYCOL; EDETATE DISODIUM; ISOPROPYL ALCOHOL; SODIUM HYDROXIDE; PHENOXYETHANOL; SODIUM BENZOATE; SODIUM SULFITE; POTASSIUM SORBATE; CHROMIUM HYDROXIDE GREEN; HYDROLYZED JOJOBA ESTERS (ACID FORM)

Proactiv Deep Cleansing Wash

Drug Facts

Active Ingredient

Salicylic Acid 2%

Purpose

Acne Treatment

Use

For the management of acne

Warnings

For external use only

When using this product

- skin irritation and dryness are more likely to occur if you use another topical acne medication at the same time. If irritation occurs, only use one topical acne medication at a time.
- avoid contact with eyes. If contact occurs, rinse eyes thoroughly with water.

Stop use and ask a doctor ifirritation becomes severe.

Keep out of reach of children.If swallowed, get medical help or contact a Poison Control Center right away.

Directions

- Sensitivity Test for a New User:Apply product sparingly to one or two small affected areas during the first 3 days. If no discomfort occurs, follow the directions stated below.
- apply a small amount to dampened skin.
- cover the entire affected area with a thin layer and rinse thoroughly. Shake before use.
- because excessive drying of the skin may occur, start with one application every other day, then gradually increase to one application daily or as directed by a doctor.
- if bothersome dryness or peeling occurs, reduce application use to every other day.

Inactive Ingredients

Water, Cocamidopropyl Betaine, Distearyl Phthalic Acid Amide, Paraffin, Stearyl Alcohol, Cetyl Alcohol, Jojoba Esters, Sodium Chloride, Sodium Methyl Cocoyl Taurate, Aloe Barbadensis Leaf Juice, Camellia Sinensis Leaf Extract, Coconut Acid, Menthol, PEG-120 Methyl Glucose Dioleate, Caprylyl Glycol, Hexylene Glycol, Ethylhexylglycerin, Ascorbic Acid, Citric Acid, Butylene Glycol, Disodium EDTA, Isopropyl Alcohol, Sodium Hydroxide, Phenoxyethanol, Sodium Benzoate, Sodium Sulfite, Potassium Sorbate, Fragrance, Chromium Hydroxide Green

Questions or comments?
Within US 1-800-950-4695

PRINCIPAL DISPLAY PANEL - 89 mL Carton

proactiv®

DEEP
CLEANSING
WASH

3 FL. OZ. 89 mL

salicylic acid acne treatment

Dist. by: The Proactiv Company LLC
100 N Sepulveda Blvd., El Segundo, CA 90245
proactiv.com ● Made in the USA
of Foreign and Domestic Components
Proactiv is a trademark of The Proactiv Company Sàrl.

PRINCIPAL DISPLAY PANEL - 267 mL Tube

proactiv®

DEEP
CLEANSING
WASH

9 FL. OZ. 267 mL

salicylic acid acne medication
Distributed by The Proactiv Company LLC
100 N Sepulveda Blvd., El Segundo, CA 90245 ● proactiv.com
Made in the USA of Foreign and Domestic Components
Proactiv is a trademark of The Proactiv Company Sàrl.

PRINCIPAL DISPLAY PANEL - 475 mL Tube

proactiv®

DEEP
CLEANSING
WASH

16 FL. OZ. 475 mL

salicylic acid acne medication